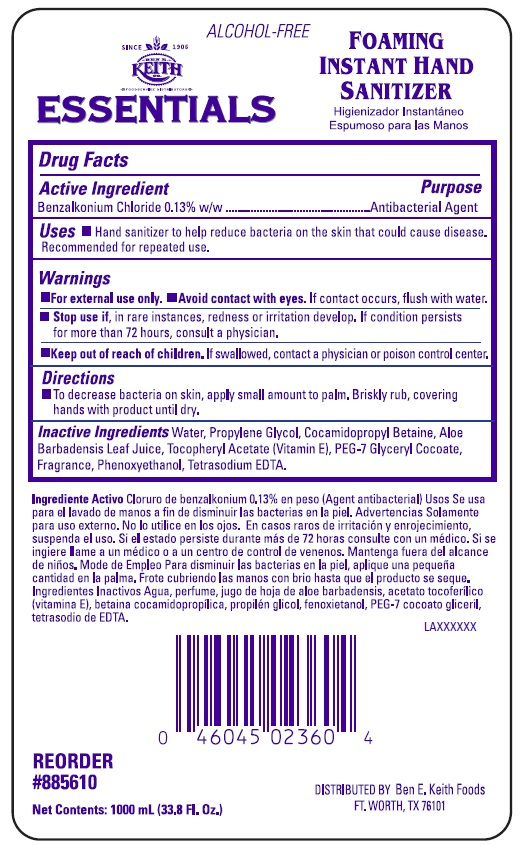 DRUG LABEL: Ben E. Keith FIHS
NDC: 50980-207 | Form: SOLUTION
Manufacturer: Ben E. Keith Foods
Category: otc | Type: HUMAN OTC DRUG LABEL
Date: 20250303

ACTIVE INGREDIENTS: BENZALKONIUM CHLORIDE 1.3 mg/1 mL
INACTIVE INGREDIENTS: WATER; EDETATE SODIUM; COCAMIDOPROPYL BETAINE; PEG-7 GLYCERYL COCOATE; PROPYLENE GLYCOL; PHENOXYETHANOL; ALOE VERA LEAF; .ALPHA.-TOCOPHEROL ACETATE, DL-

Drug Facts

Active Ingredient

Benzalkonium Chloride 0.13% w/w

Purpose

Antibacterial Agent

Uses

Hand sanitizer to help reduce bacteria on the skin that could cause disease. Recommended for repeated use.

Warnings

- For external use only

DO NOT USE

- Avoid contact with eyes

WHEN USING

Avoid contact with eyes. If contact occurs, flush with water.

Stop use if, in rare instances, redness or irritation develop. If condition persists for more than 72 hours, consult a physician.

Keep out of reach of children. If swallowed, contact a physician or poison control center.

Directions

- To decrease bacteria on skin, apply small amount to palm. Briskly rub, covering hands with product until dry.

INACTIVE INGREDIENT

Inactive Ingredients Water, Propylene Glycol, Cocamidopropyl Betaine, Aloe Barbadensis Leaf, Tocopheryl Acetate (Vitamin E), PEG-7 Glyceryl Cocoate, Fragrance, Phenoxyethanol, Tetrasodium EDTA.

Representative label and principal display panel

ALCOHOL-FREE

BEN E. KEITH

ESSENTIALS

FOAMINIG

INSTANT HAND

SANITIZER

REORDER

#885610

Net Contents: 1000 mL (33.8 Fl. Oz.)

DISTRIBUTED BY Ben E. Keith Foods

FT. WORTH, TX 76101